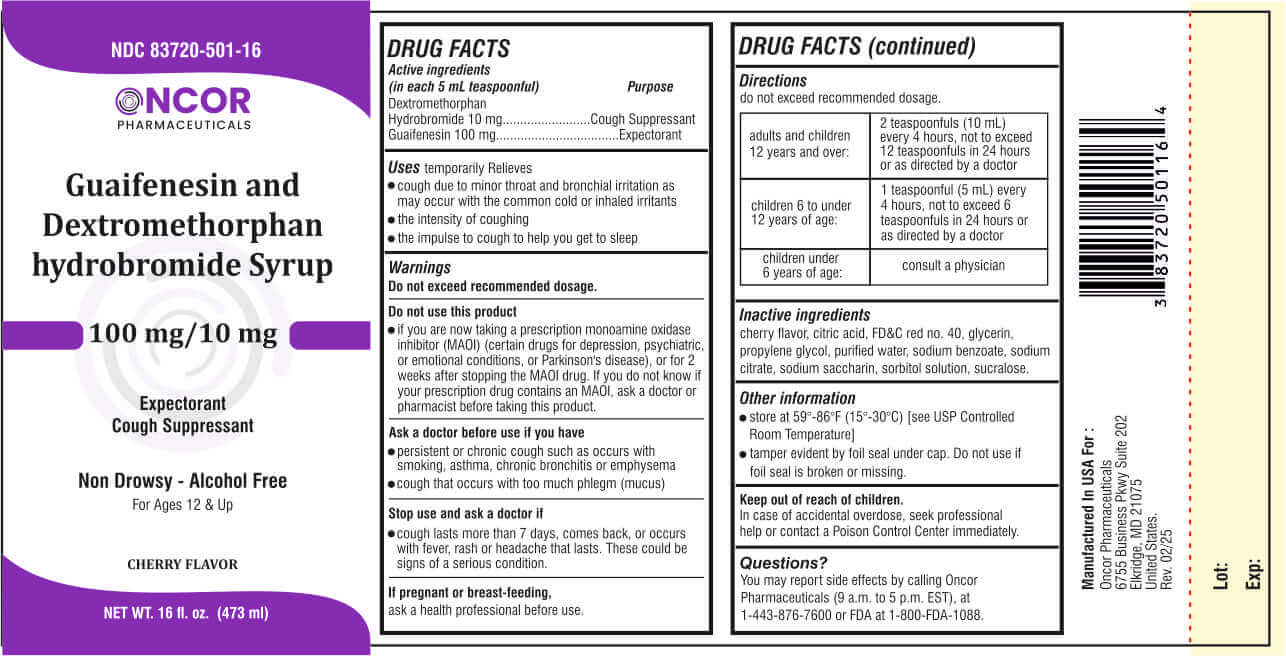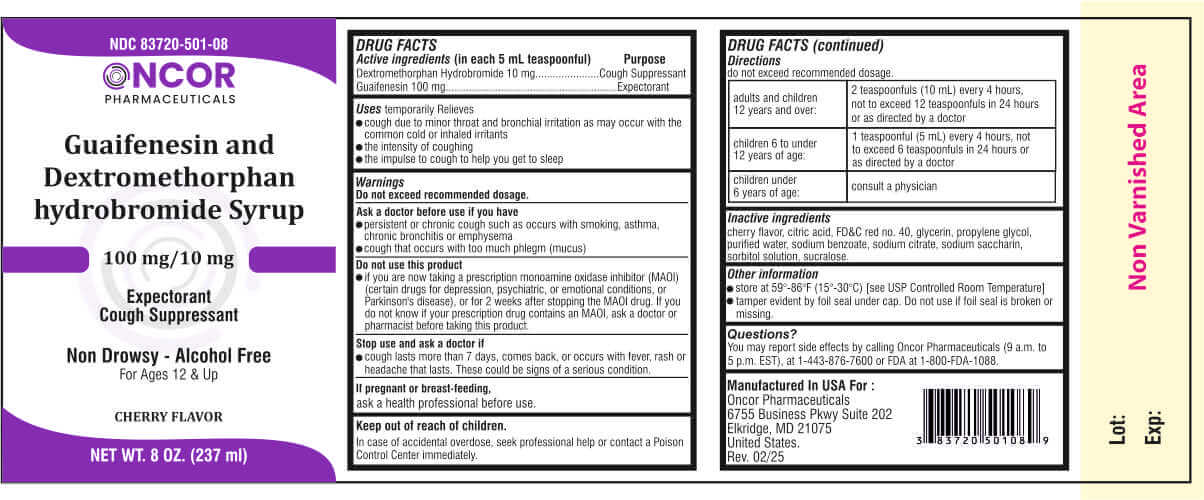 DRUG LABEL: Guaifenesin and Dextromethorphan hydrobromide
NDC: 83720-501 | Form: LIQUID
Manufacturer: Oncor Pharmaceuticals
Category: otc | Type: HUMAN OTC DRUG LABEL
Date: 20250212

ACTIVE INGREDIENTS: DEXTROMETHORPHAN HYDROBROMIDE 10 mg/5 mL; GUAIFENESIN 100 mg/5 mL
INACTIVE INGREDIENTS: CITRIC ACID; FD&C RED NO. 40; GLYCERIN; PROPYLENE GLYCOL; WATER; SODIUM BENZOATE; SODIUM CITRATE; SODIUM SACCHARIN; SORBITOL SOLUTION; CHERRY; SUCRALOSE

Guaifenesin and Dextromethorphan hydrobromide

Active ingredients

(in each 5 mL teaspoonful) Purpose

Dextromethorphan Hydrobromide 10 mg...........Cough Suppressant
Guaifenesin 100 mg.............................................Expectorant

Uses

temporarily Relieves

- cough due to minor throat and bronchial irritation as may occur with the common cold or inhaled irritants

- the intensity of coughing

- the impulse to cough to help you get to sleep

Warnings

Do not exceed recommended dosage.

Do not use this product

If you are now taking a prescription monoamine oxidase inhibitor (MAOI) (certain drugs for depression, psychiatric, or emotional conditions, or Parkinson's disease), or for 2 weeks after stopping the MAOI drug. If you do not know if your prescription drug contains an MAOI, ask a doctor or pharmacist before taking this product.

Ask a doctor before use if you have

- persistent or chronic cough such as occurs with smoking, asthma, chronic bronchitis or emphysema

- cough that occurs with too much phlegm (mucus)

Stop use and ask a doctor if

- cough lasts more than 7 days, comes back, or occurs with fever, rash or headache that lasts. These could be signs of a serious condition.

If pregnant or breast-feeding,

ask a health professional before use.

Directions

do not exceed recommended dosage.

adults and children 12 years and over: | 2 teaspoonfuls (10 mL) every 4 hours, not to exceed 12 teaspoonfuls in 24 hours or as directed by a doctor
children 6 to under 12 years of age: | 1 teaspoonful (5 mL) every 4 hours, not to exceed 6 teaspoonfuls in 24 hours or as directed by a doctor
children under 6 years of age: | consult a physician

Inactive ingredients

cherry flavor, citric acid, FD&C red no. 40, glycerin, propylene glycol, purified water, sodium benzoate, sodium citrate, sodium saccharin, sorbitol solution, sucralose.

Other information

- store at 59°-86°F (15°-30°C) [see USP Controlled Room Temperature]

- tamper evident by foil seal under cap. Do not use if foil seal is broken or missing.

Keep out of reach of children.

OVERDOSAGE

In case of accidental overdose, seek professional help or contact a Poison Control Center immediately.

Questions?

You may report side effects by calling Oncor Pharmaceuticals (9 a.m. to 5 p.m. EST), at 1-443-876-7600 or FDA at 1-800-FDA-1088.

Principal Display Panel

Oncor Pharmaceuticals

NDC 83720-501-16

Guaifenesin and Dextromethorphan hydrobromide USP

100 mg/10 mg

Expectorant
Cough Suppressant

Non Drowsy - Alcohol Free

For Ages 12 & Up

CHERRY FLAVOR

NET WT. 16 fl. oz. (473 ml)

NDC 83720-501-08

Guaifenesin and Dextromethorphan hydrobromide USP

100 mg/10 mg

Expectorant
Cough Suppressant

Non Drowsy - Alcohol Free

For Ages 12 & Up

CHERRY FLAVOR

NET WT. 8 OZ. (237 ml)

Manufactured In USA For :

Oncor Pharmaceuticals
6755 Business Pkwy Suite 202
Elkridge, MD 21075
United States.
Rev. 02/25